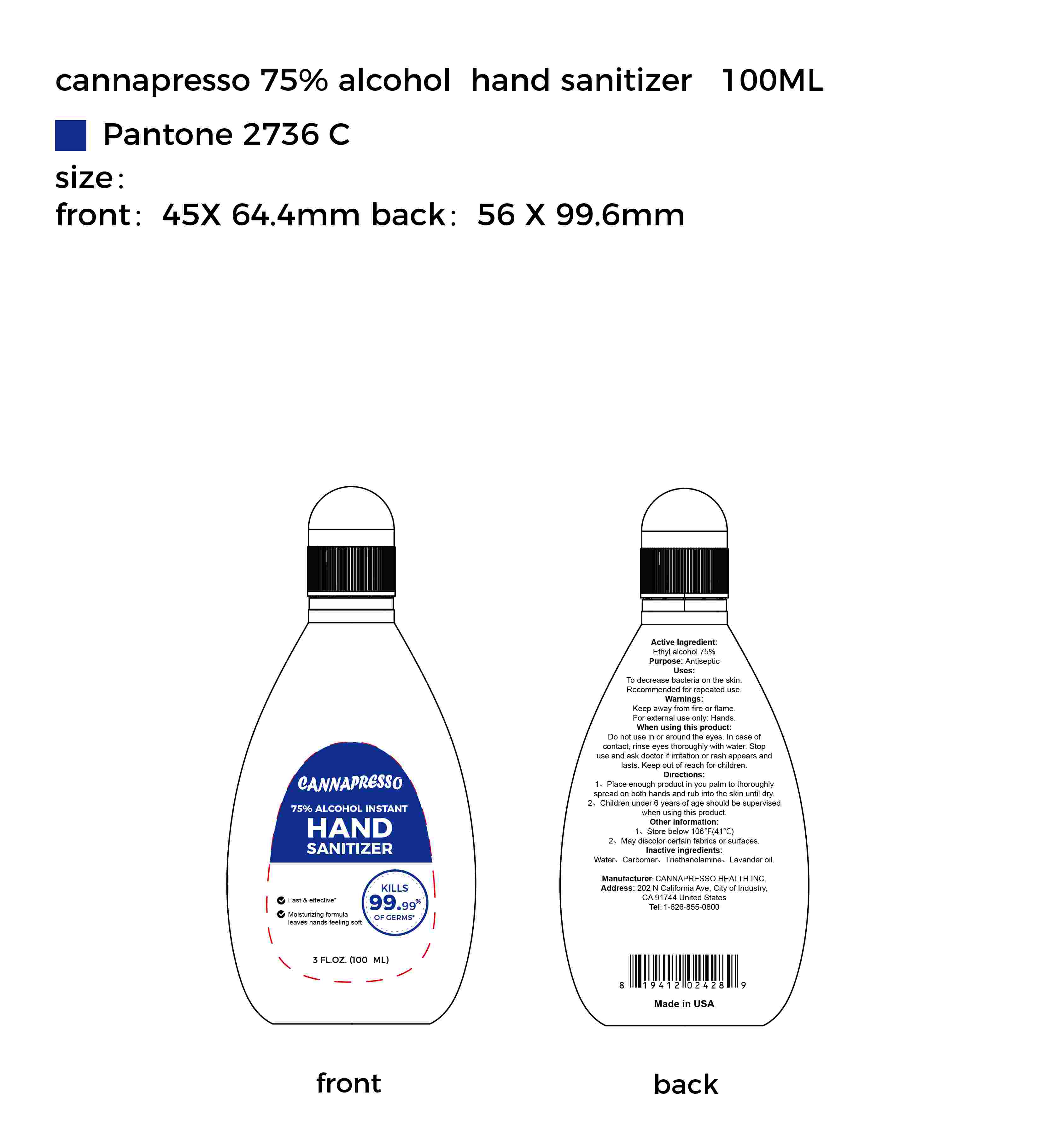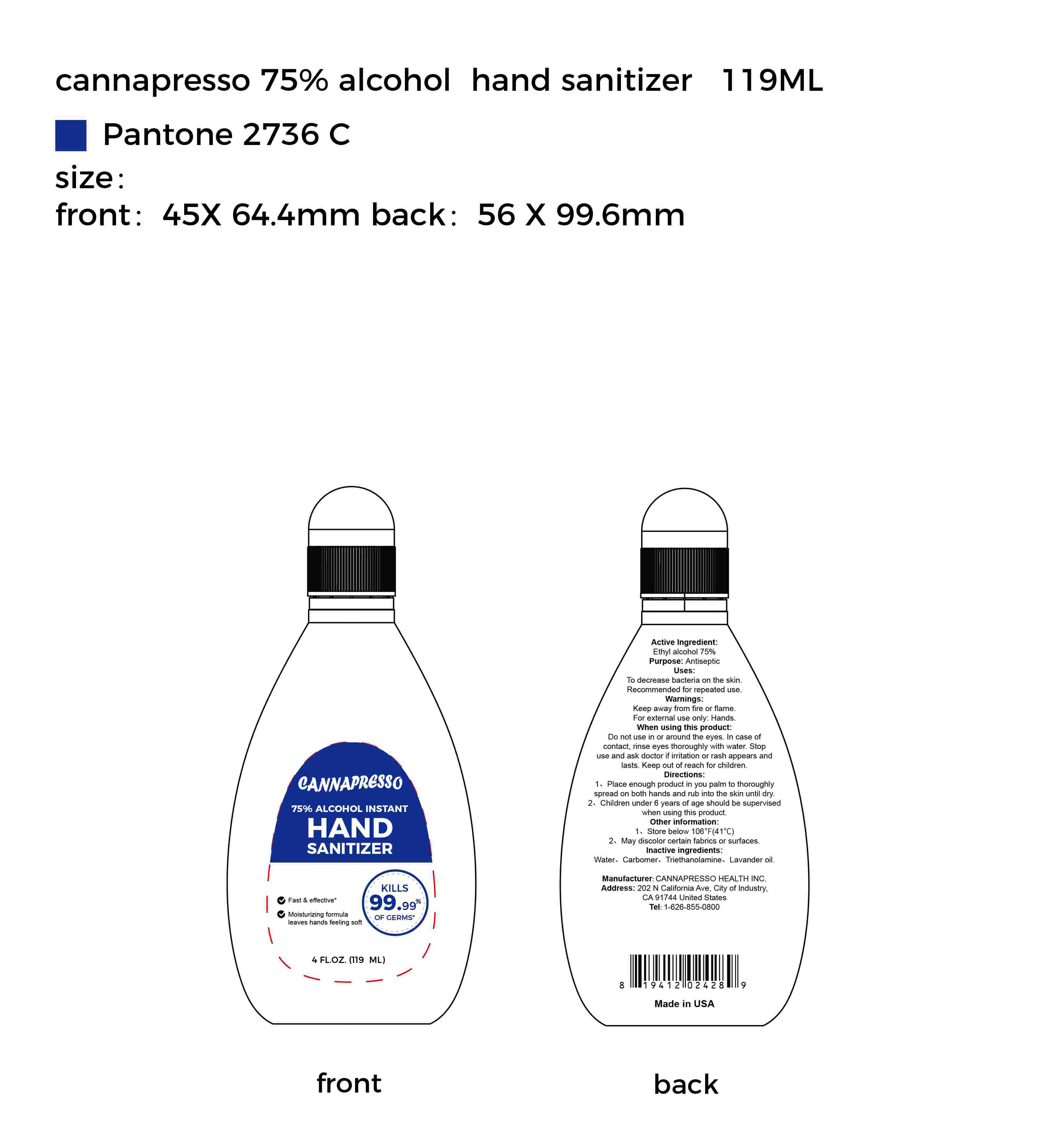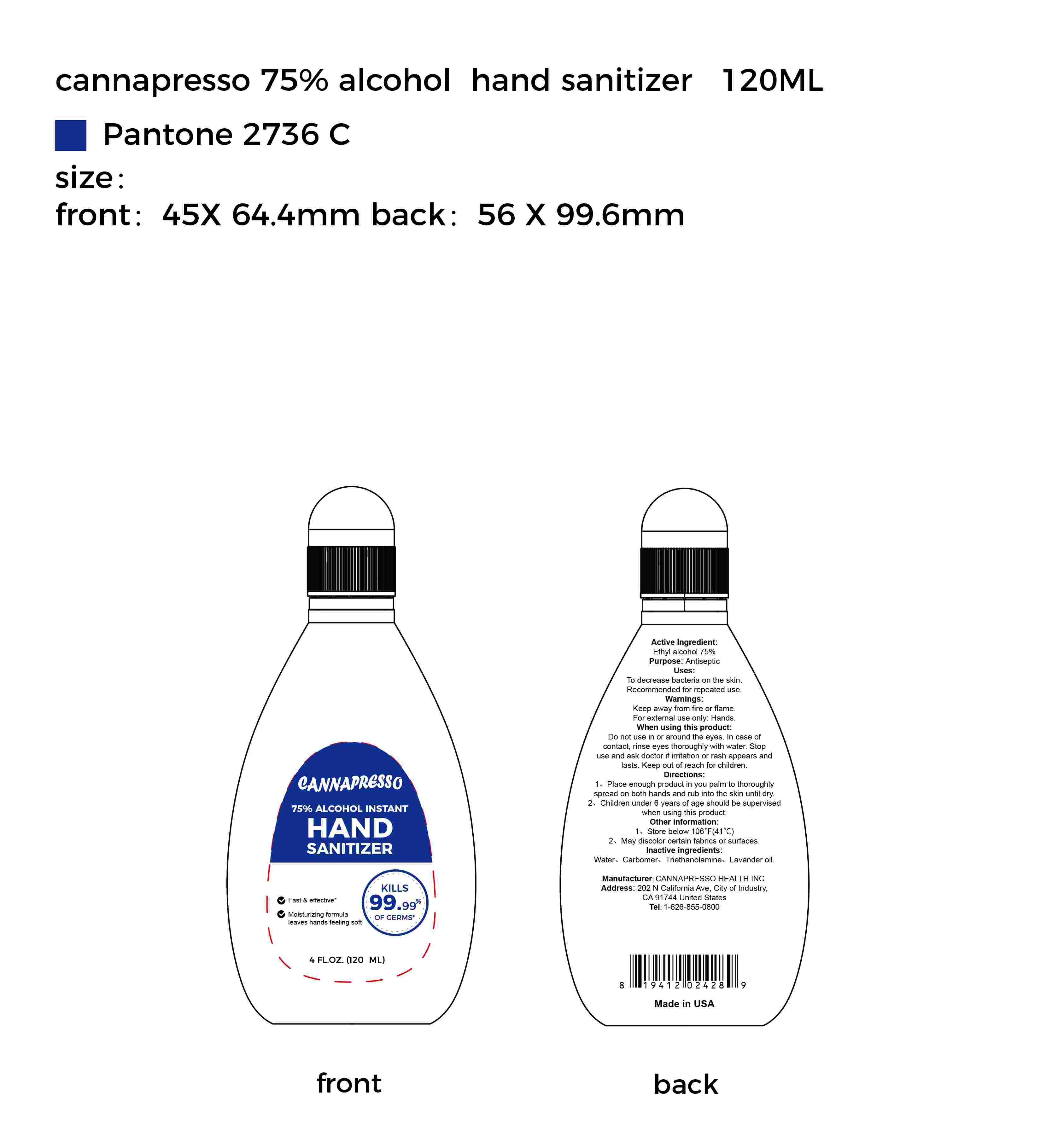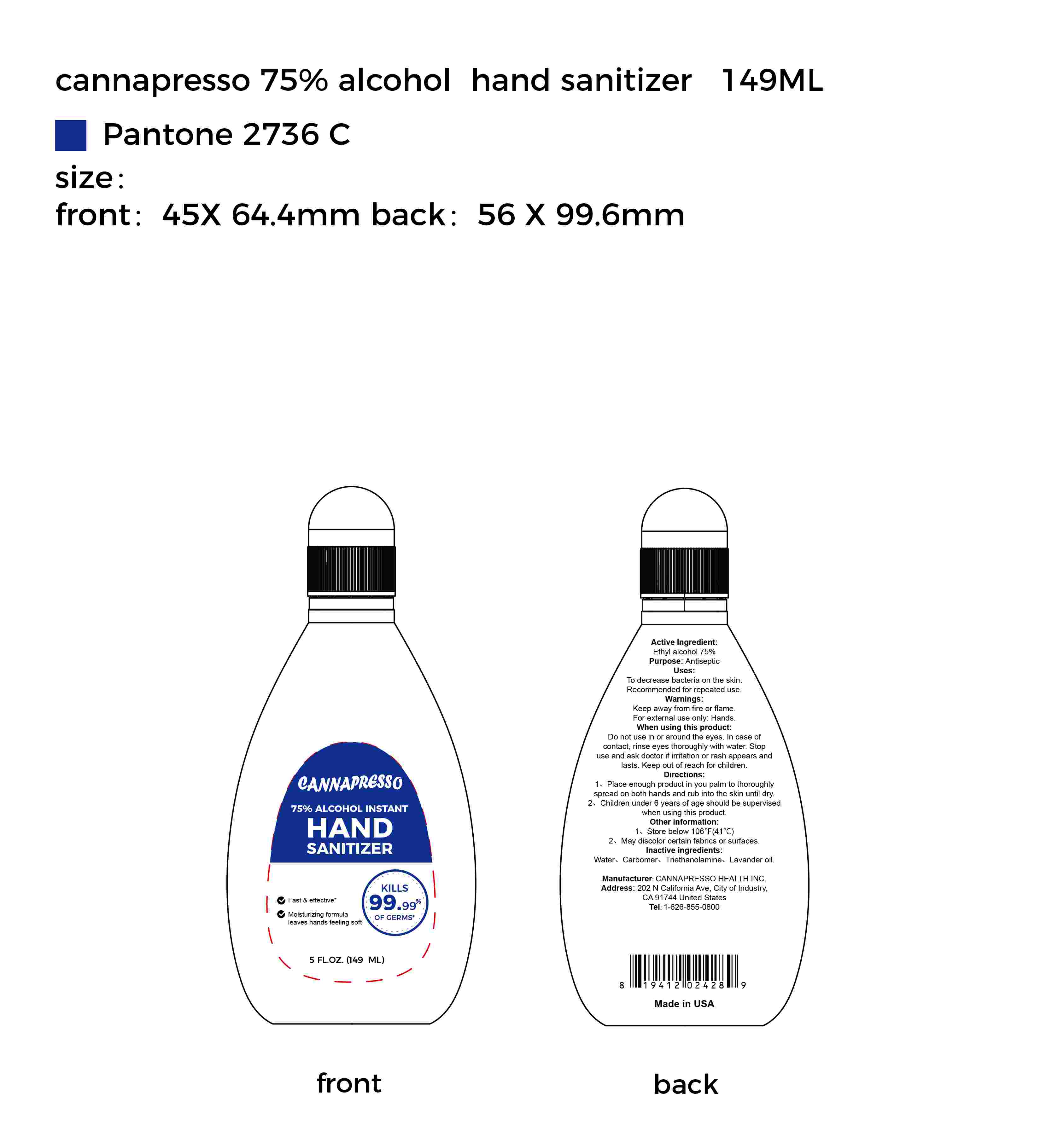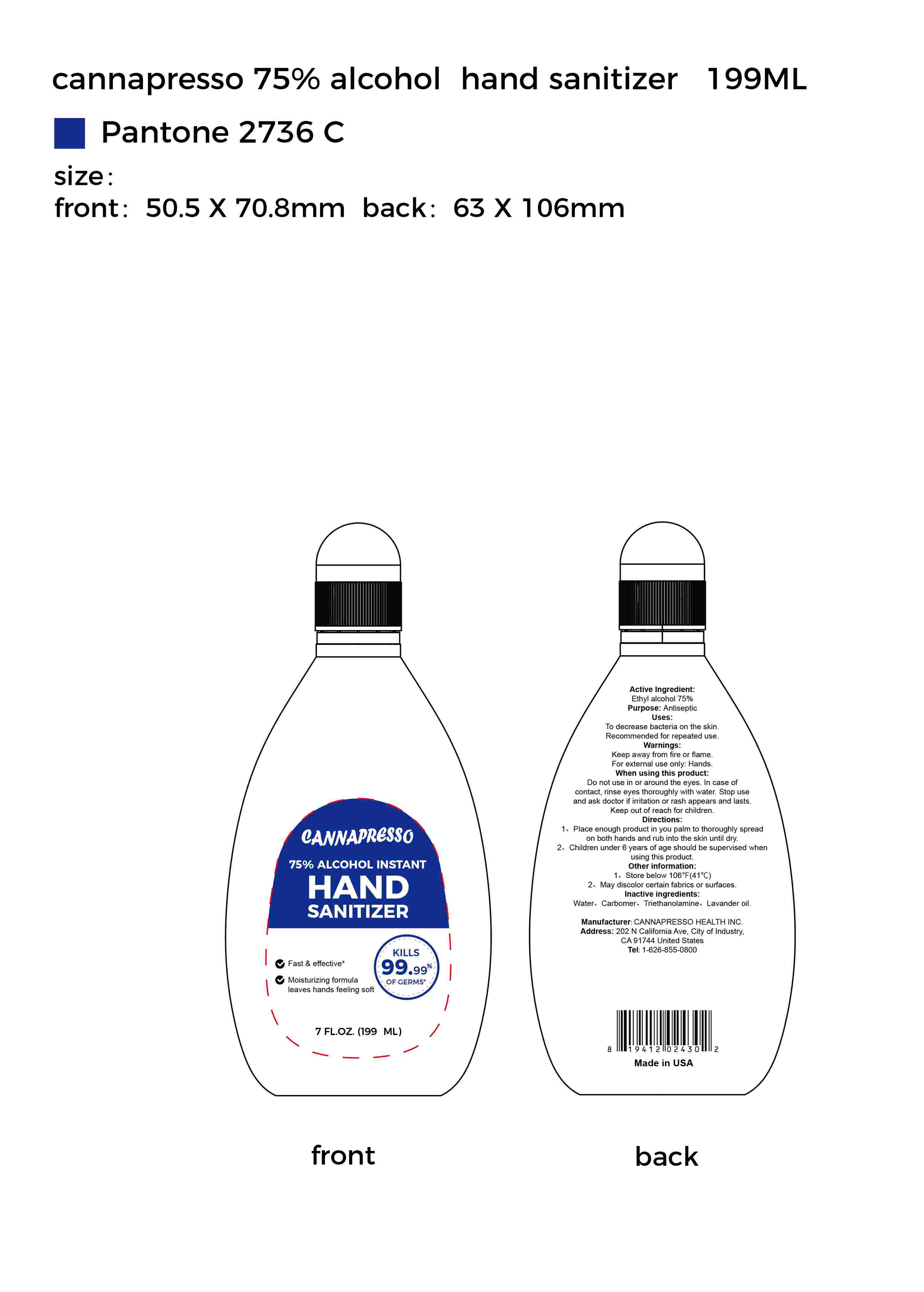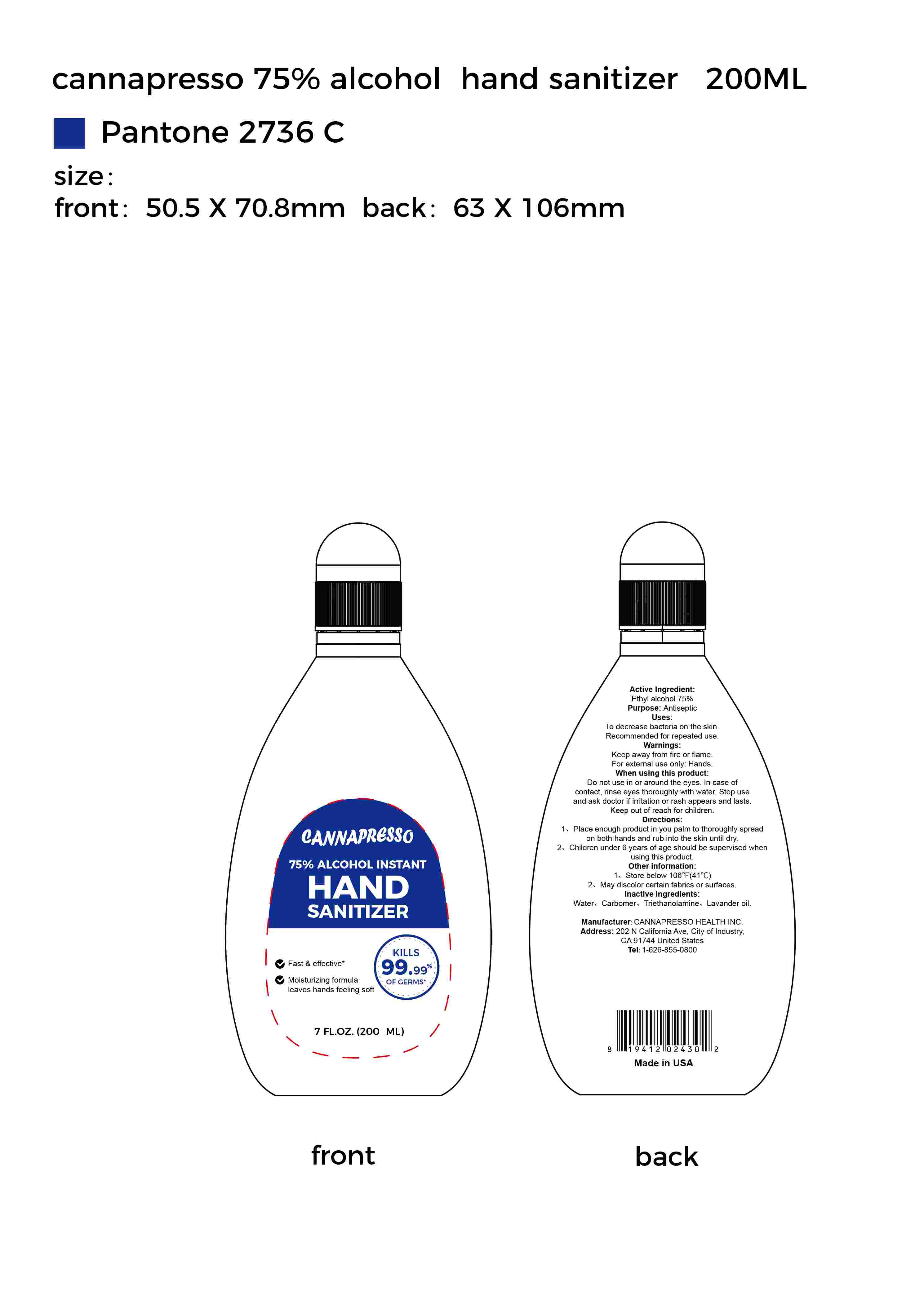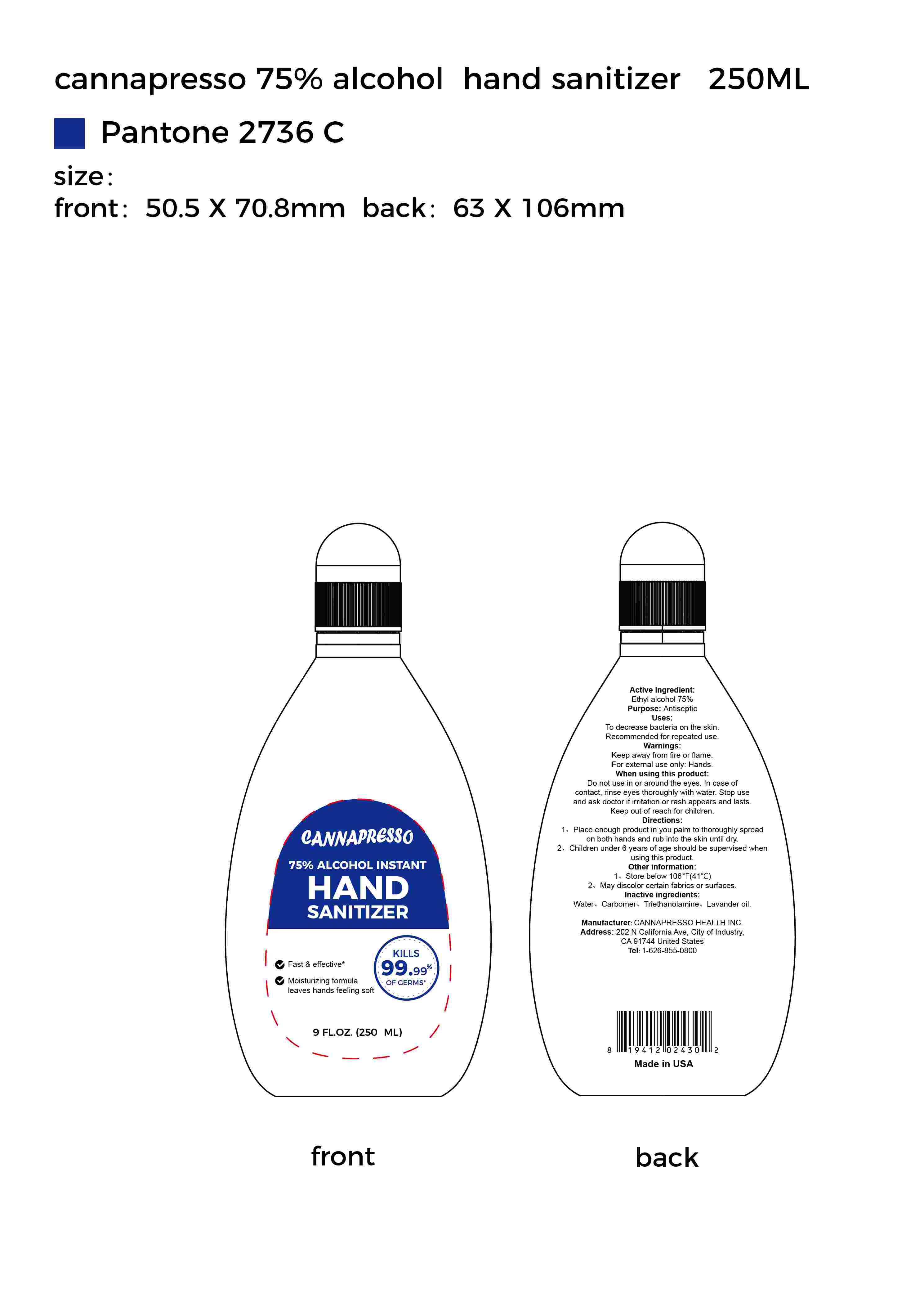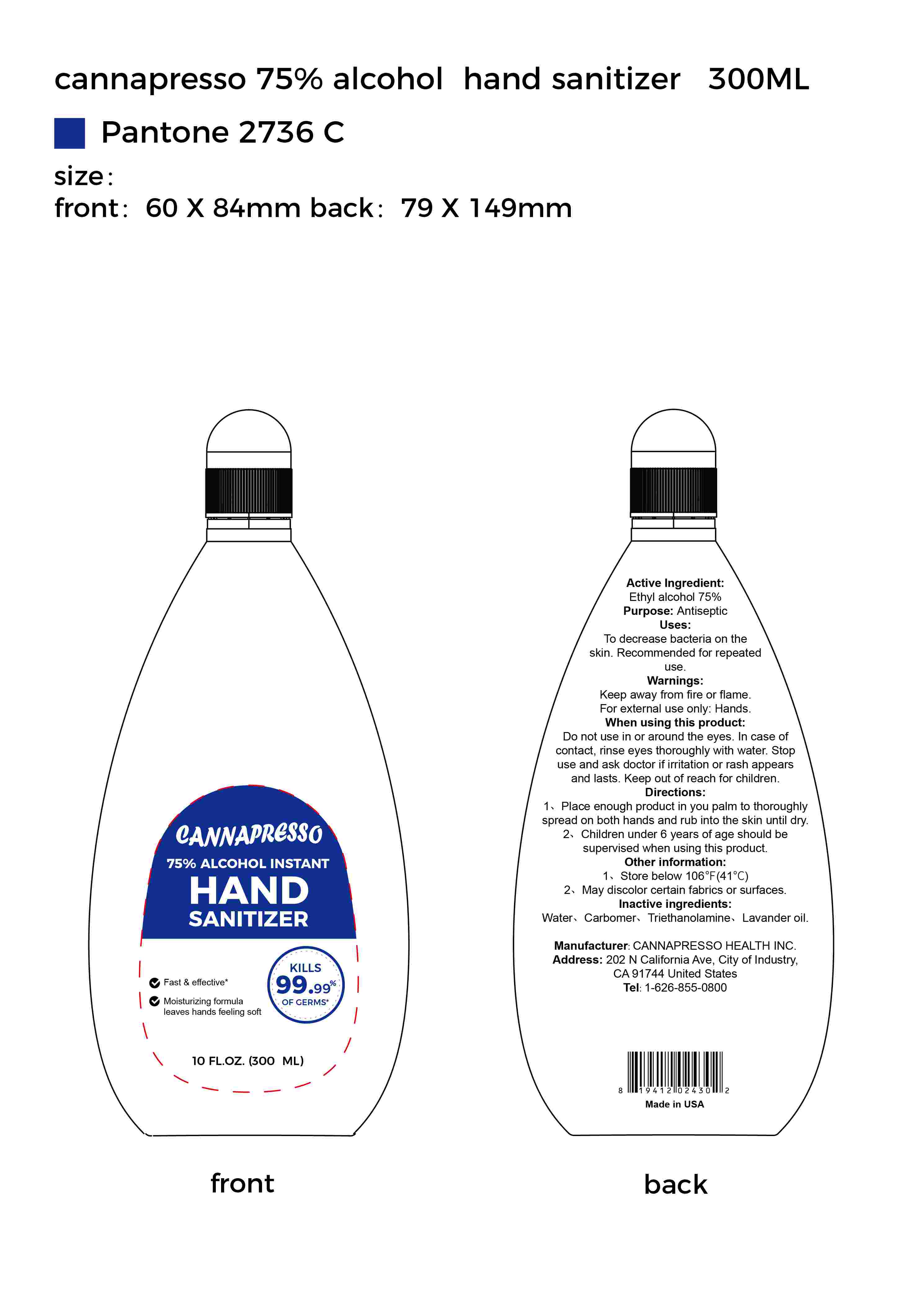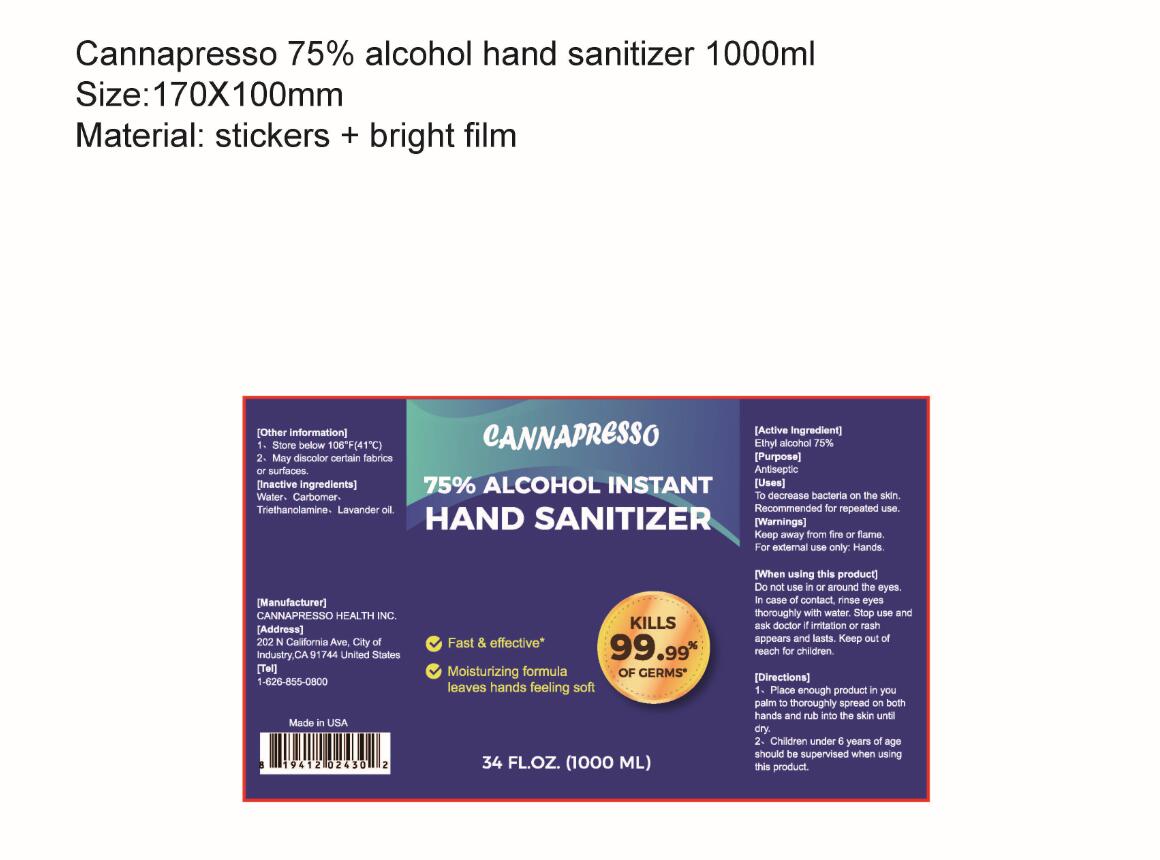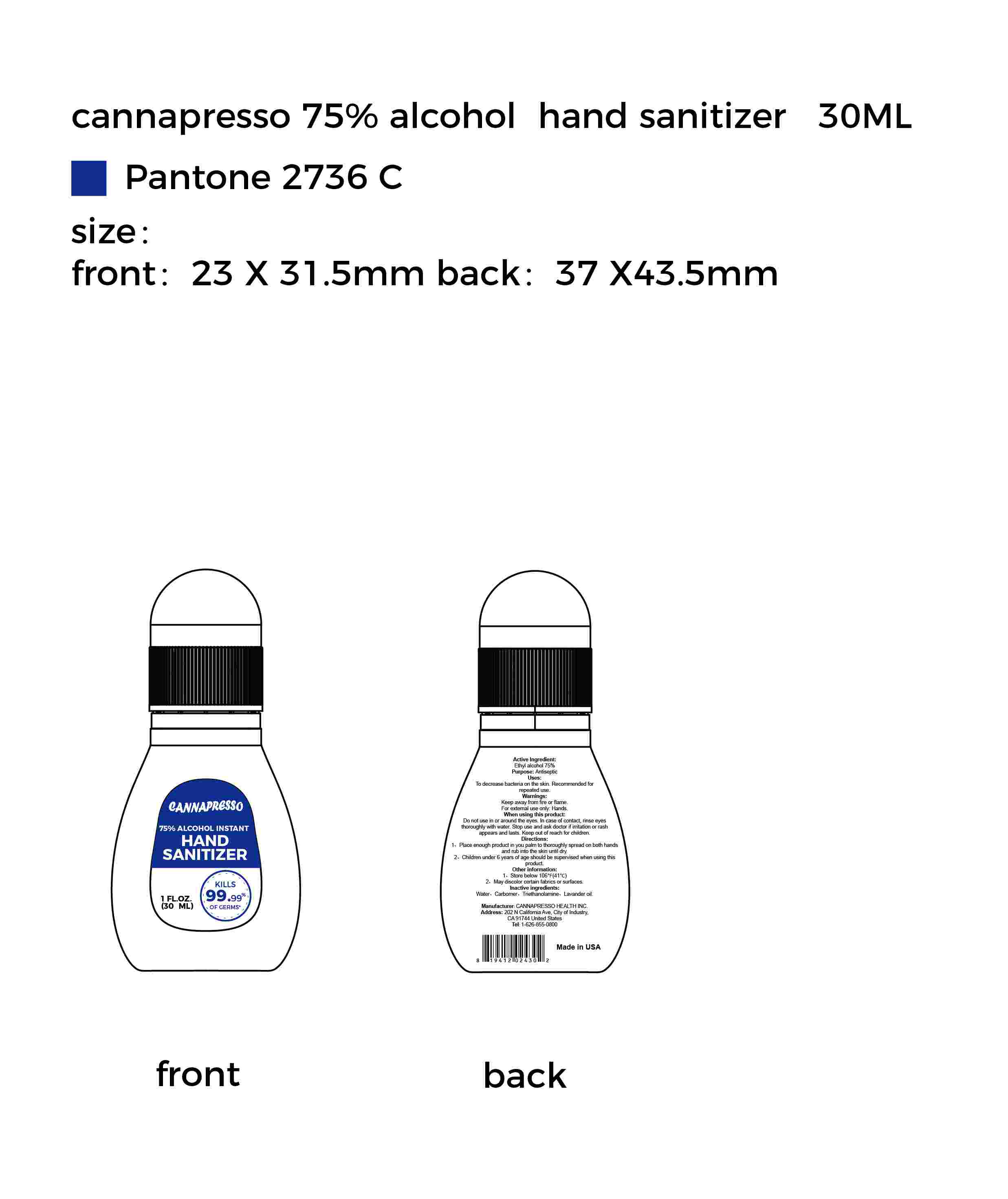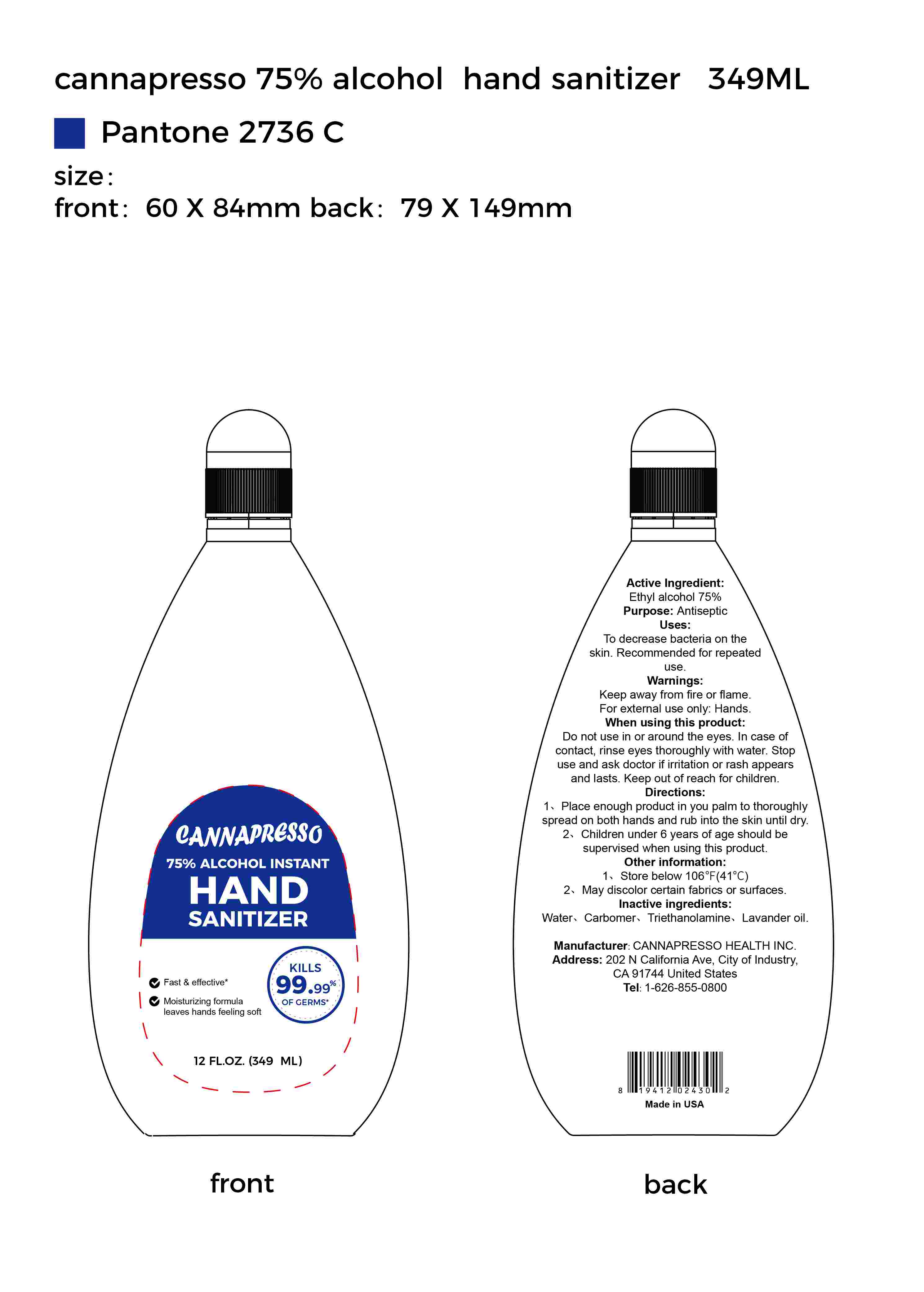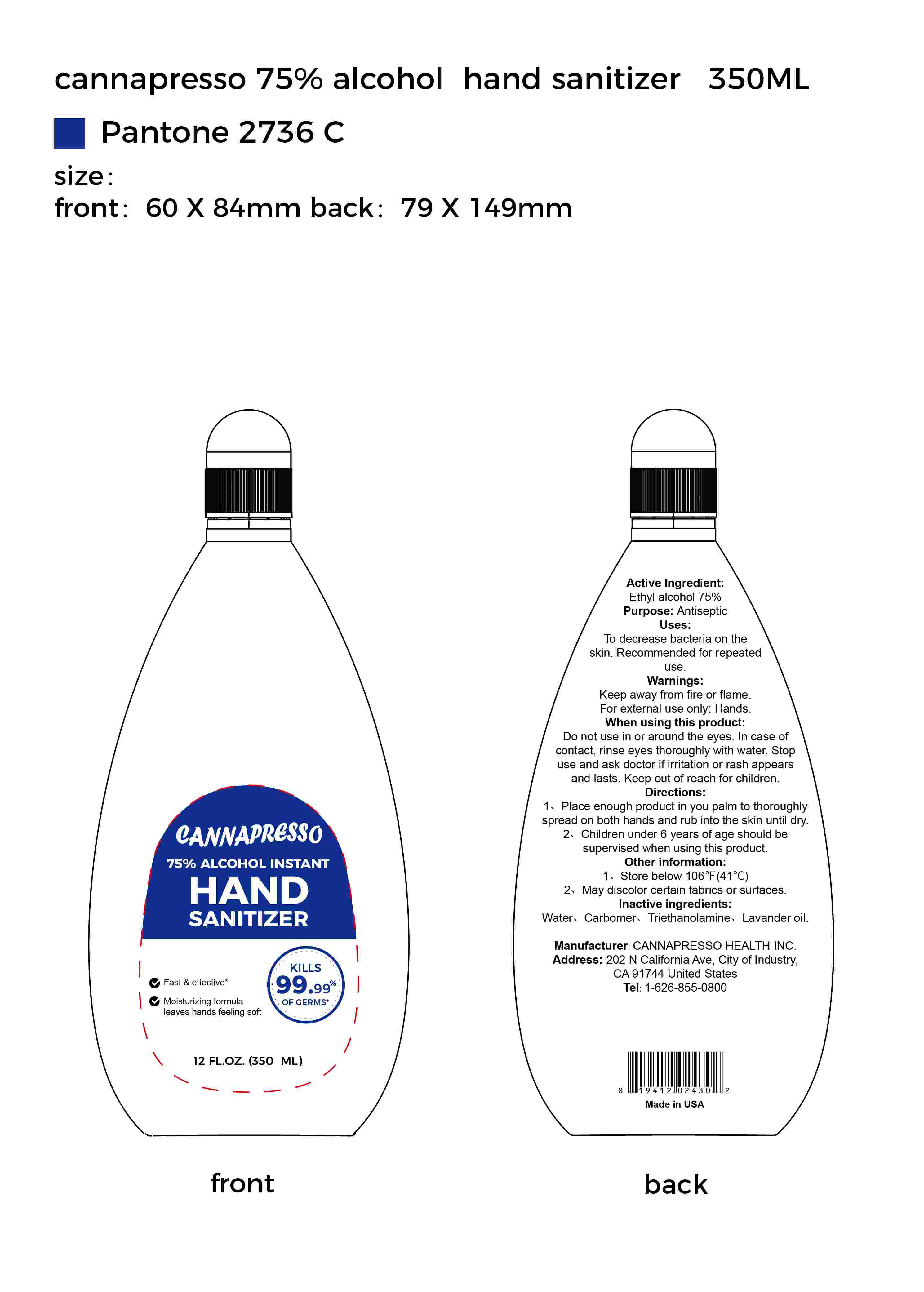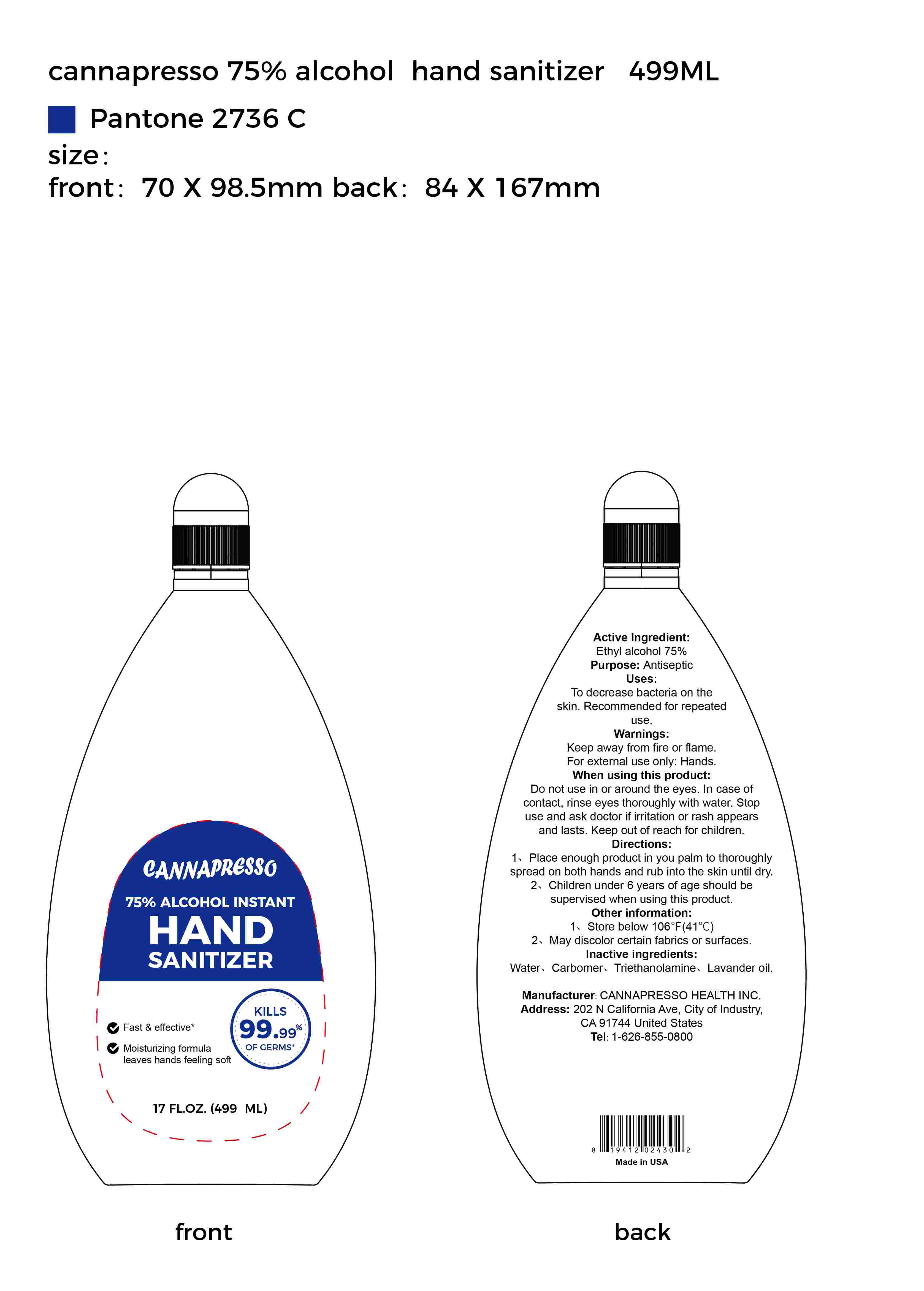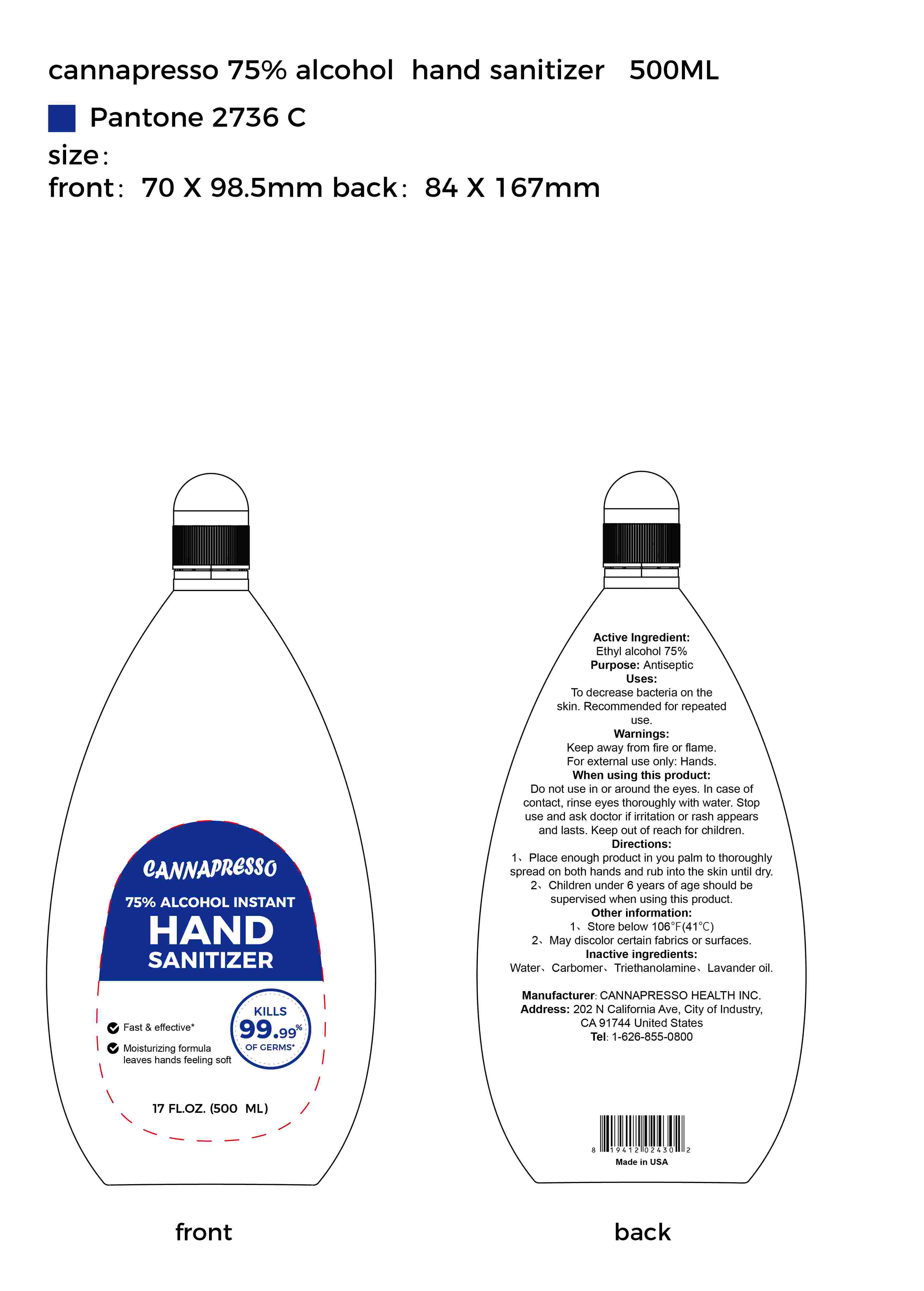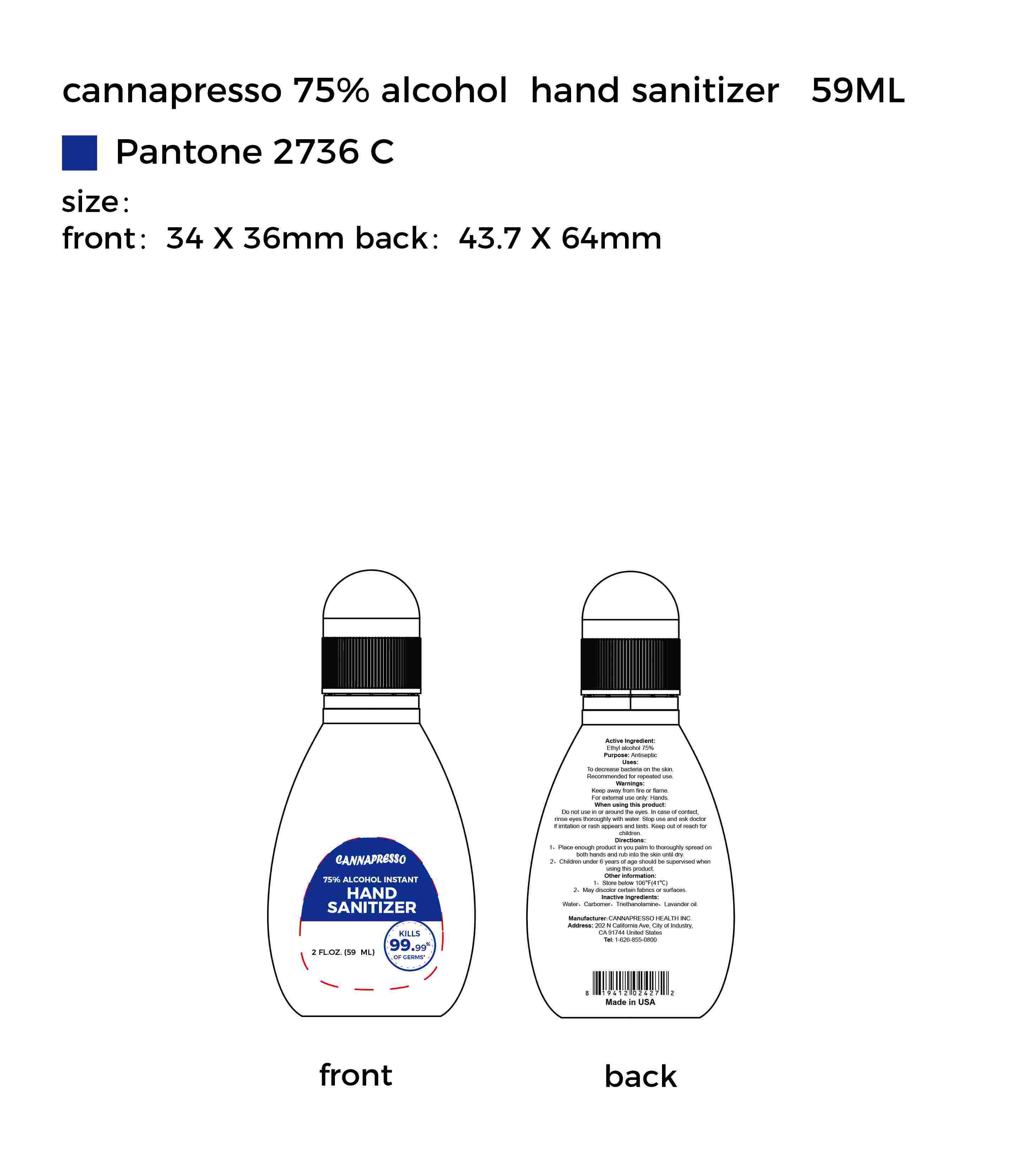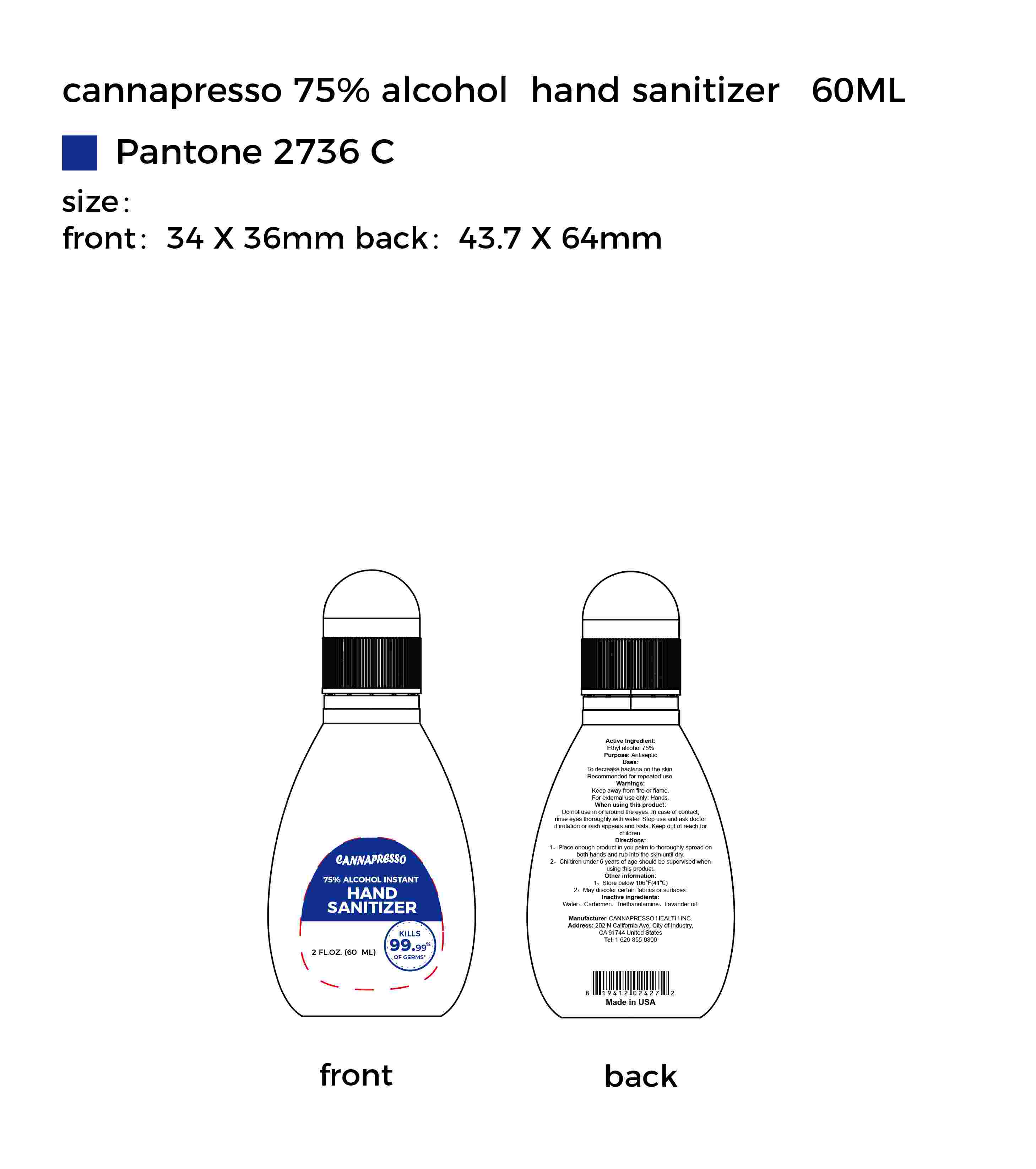 DRUG LABEL: 75% Alcohol Instant Hand Sanitizer
NDC: 75242-007 | Form: GEL
Manufacturer: Cannapresso Health. Inc.
Category: otc | Type: HUMAN OTC DRUG LABEL
Date: 20200520

ACTIVE INGREDIENTS: ALCOHOL 75 mL/100 mL
INACTIVE INGREDIENTS: LAVENDER OIL; CARBOMER HOMOPOLYMER, UNSPECIFIED TYPE; TROLAMINE; WATER

Active Ingredient(s)

Ethyl Alcohol 75%

Purpose

Antiseptic

Use

To decrease bacteria on the skin.
Recommended for repeated use.

Warnings

Keep away from fire or flame.
For external use only: Hands

Do not use in or around the eyes. In case of contact, rinse eyes thoroughly with water.

Do not use in or around the eyes. In case of contact, rinse eyes thoroughly with water. Stop use and ask doctor if irritation or rash appears and lasts. Keep out of reach for children.

Stop use and ask doctor if irritation or rash appears and lasts.

Keep out of reach for children.

Directions

1, Place enough product in you palm to thoroughly spread on both hands and rub into the skin until dry.
2, Children under 6 years of age should be supervised when using this product.

Other information

1, Store below 106F(41°C).
2, May discolor certain fabrics or surfaces.

Inactive ingredients

Water,Carbomer,Triethanolamine,Lavander oil